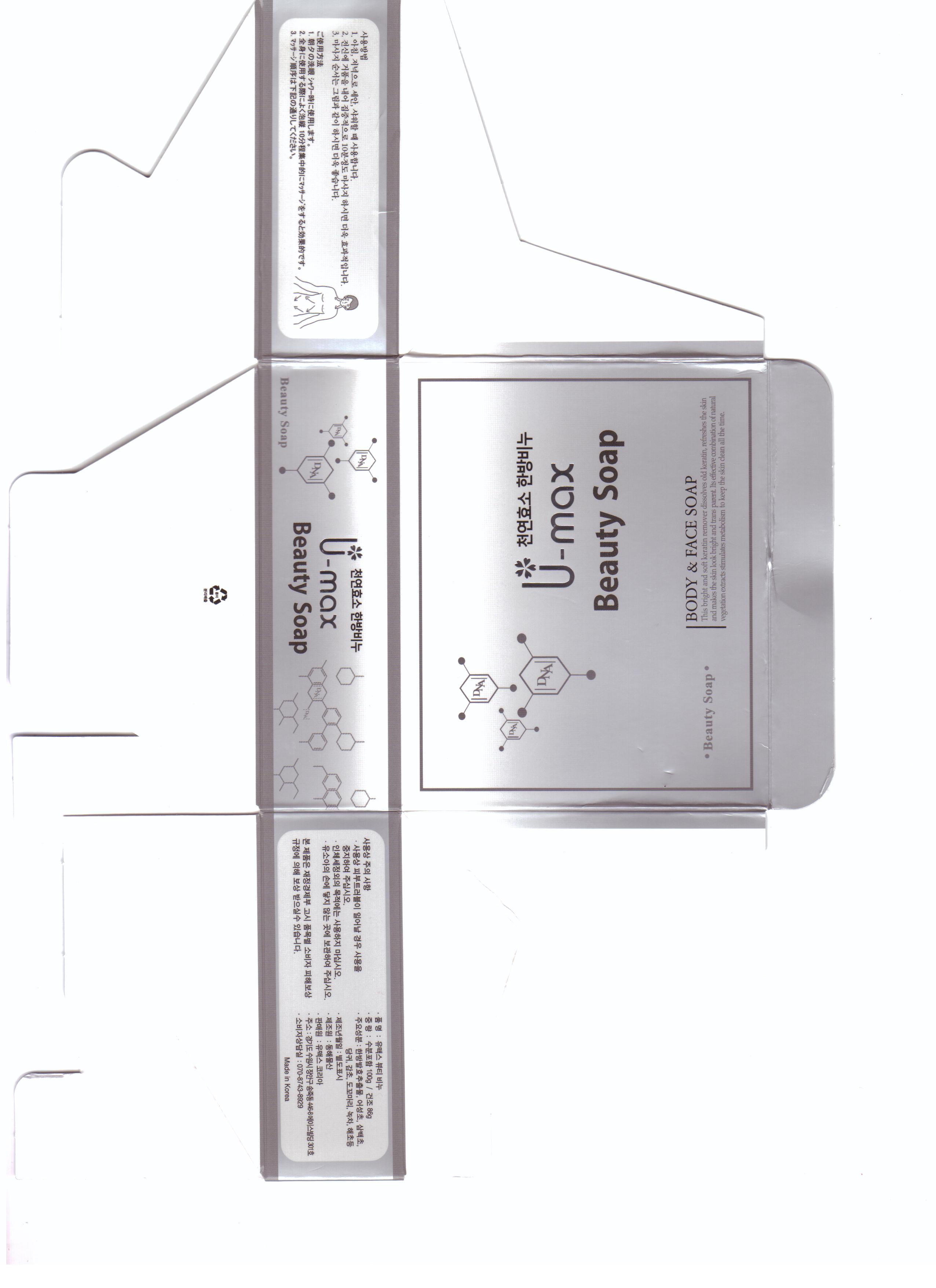 DRUG LABEL: U-max Beauty
NDC: 50795-4001 | Form: SOAP
Manufacturer: VS Shinbi Co., Ltd.
Category: otc | Type: HUMAN OTC DRUG LABEL
Date: 20120612

ACTIVE INGREDIENTS: CHITOSAN MEDIUM MOLECULAR WEIGHT (200-800 MPA.S) 1 g/100 g
INACTIVE INGREDIENTS: HOUTTUYNIA CORDATA FLOWERING TOP; SAURURUS CHINENSIS FLOWER; ARTEMISIA ABROTANUM WHOLE; ANGELICA ARCHANGELICA ROOT; KELP BASS; ROSA GALLICA FLOWER OIL; GLYCOL OLEATE; ALOE

Drug Facts

active ingredient: chitosan

inactive ingredient: houttuynia, saururus, chinensis, herbacea, green tes, artemisia, angelicae, kelp, rose oil, glycol, aloe extract, perfume

PURPOSE

skin protectant,

keep out of reach of the children

INDICATIONS AND USAGE

- apply only for skin
- apply 2 or 3 times a day and wash away with water

WARNINGS

- keep out of eyes, ears and mouth
- if contact occurs, rinse away with plenty of water

DOSAGE AND ADMINISTRATION

- for external use only